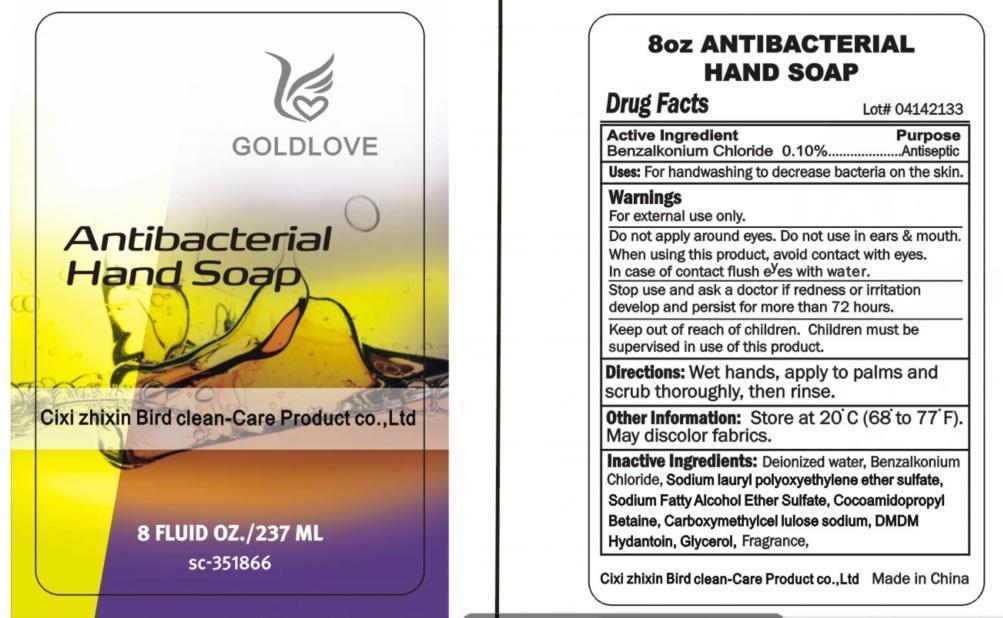 DRUG LABEL: Ultracruz Antibacterial Hand
NDC: 49877-012 | Form: SOAP
Manufacturer: Cixi Zhixin Bird Clean-care Product Co., Ltd.
Category: otc | Type: HUMAN OTC DRUG LABEL
Date: 20140822

ACTIVE INGREDIENTS: BENZALKONIUM CHLORIDE 0.1 g/100 mL
INACTIVE INGREDIENTS: WATER 72.525 g/100 mL; DMDM HYDANTOIN; CARBOXYMETHYLCELLULOSE SODIUM; GLYCEROL FORMAL; LAURAMIDOPROPYL BETAINE; SODIUM LAURETH SULFATE

Antibacterial Hand Soap

Active Ingredient:

Benzalkonium Chloride 0.1%

Purpose:

Antiseptic

Uses:

For hand washing to kill bacterial on the skin

Warnings

For external use only

Flammable. Keep away from fire or flame

Do not apply around eyes. Do not use in ears & mouth

When using this product, avoid contatc with eyes. In case of contact, flush eyes with water

Stop use and see a doctor if irritation or redness develop and persist for more than 72 hours

Keep out of reach of children. Children must be supervised in use of this product.

Directions:

Wet hands, apply to palms, scrub thoroughly, then rinse.

Other Information:

Store at 20C (68-77F). May discolor fabrics

Inactive Ingredient:

Deionized water, Sodium lauryl polyoxyehthylene ether sulfate, Sodium fatty alcohol ethyl sulfate, Cocoamidoprophyl

betaine, Carboxylmethylcellulose sodium, DMDM Hydantoin, Glycerol, Frangance